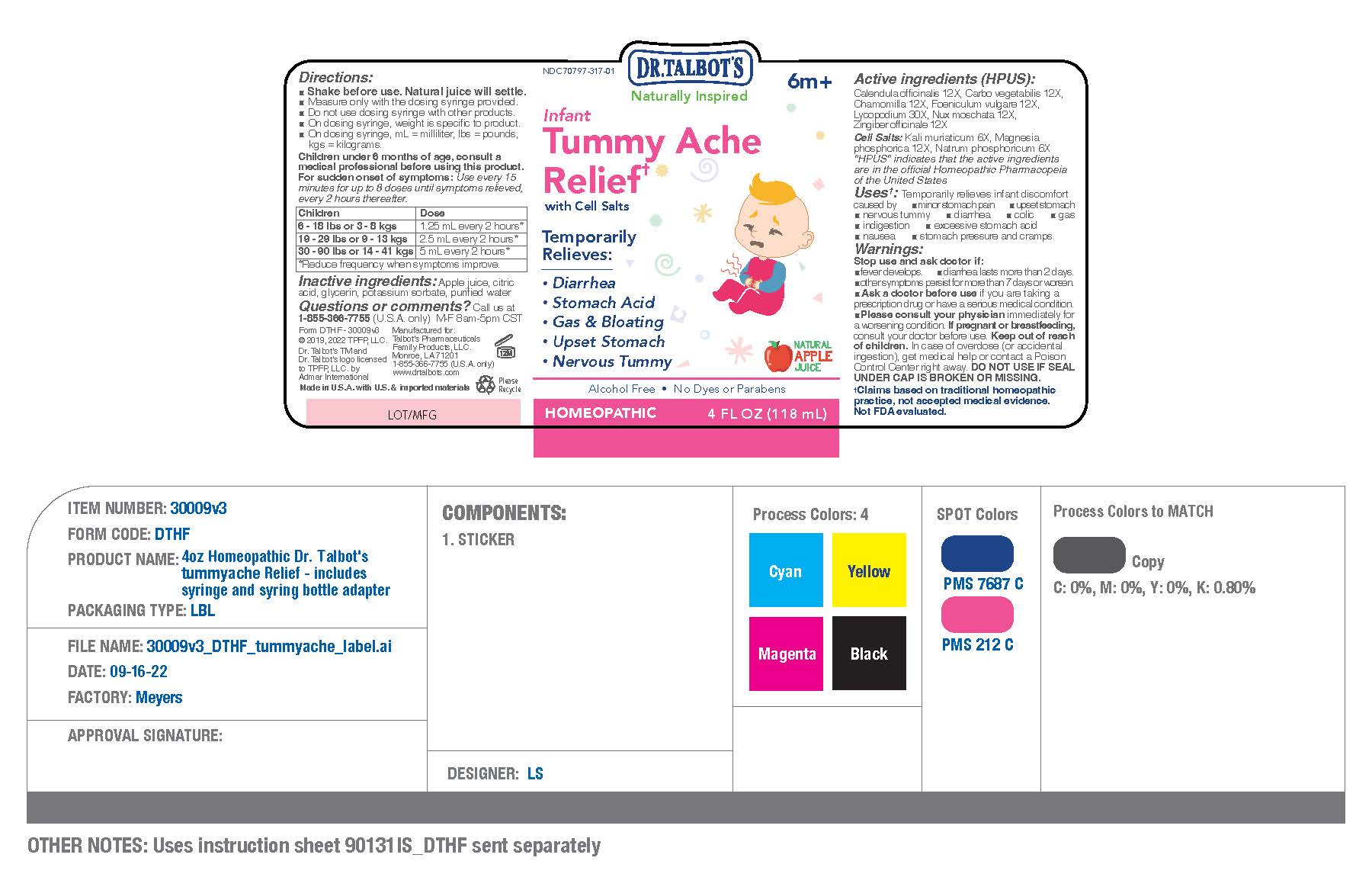 DRUG LABEL: Dr Talbots Infant Tummy Ache Relief
NDC: 70797-317 | Form: LIQUID
Manufacturer: Talbot's Pharmaceuticals Family Products,LLC.
Category: homeopathic | Type: HUMAN OTC DRUG LABEL
Date: 20220928

ACTIVE INGREDIENTS: POTASSIUM CHLORIDE 6 [hp_X]/118 mL; NUTMEG 12 [hp_X]/118 mL; LYCOPODIUM CLAVATUM SPORE 30 [hp_X]/118 mL; MAGNESIUM PHOSPHATE, DIBASIC TRIHYDRATE 12 [hp_X]/118 mL; GINGER 12 [hp_X]/118 mL; FENNEL SEED 12 [hp_X]/118 mL; SODIUM PHOSPHATE, DIBASIC, HEPTAHYDRATE 6 [hp_X]/118 mL; CALENDULA OFFICINALIS FLOWERING TOP 12 [hp_X]/118 mL; MATRICARIA CHAMOMILLA 12 [hp_X]/118 mL; ACTIVATED CHARCOAL 12 [hp_X]/118 mL
INACTIVE INGREDIENTS: WATER; GLYCERIN; POTASSIUM SORBATE; CITRIC ACID MONOHYDRATE; APPLE JUICE

Active Ingredient

Active ingredients (HPUS):

- Calendula officinalis 12X
- Carbo vegetablis 12X
- Chamomilla 12X
- Foeniculum vulgare 12X
- Lycopodium 30X
- Nux moschata 12X
- Zingiber officinalen 12X

Cell Salts:

- Kali muriaticum 6X
- Magnesia phosphorica 12X
- Natrum phosphoricum 6X

- Ask a doctor before use if you are taking a prescription drug or have a serious medical condition. condition.

Pregnant

If pregnant or breastfeeding, consult your doctor before use.

Keep Out of Reach Of Children

Keep out of reach
of children. In case of overdose (or accidental ingestion), get medical help or contact a Poison Control Center right away. DO NOT USE IF SEAL UNDER CAP IS BROKEN OR MISSING.

Inactive Ingredient

Inactive ingredients: Apple juice, citric acid, glycerin, potassium sorbate, purified water

Dosage

Children under 6 months of age, consult a medical professional before using this product.

For sudden onset of symptoms: Use every 15 minutes for up to 8 doses until symptoms relieved, every 2 hours thereafter.

Children Dose
6 - 18 lbs or 3 - 8 kgs 1.25 mL every 2 hours*
19 - 29 lbs or 9 - 13 kgs 2.5 mL every 2 hours*
30 - 90 lbs or 14 - 41 kgs 5 mL every 2 hours*
*Reduce frequency when symptoms improve.

Questions

Questions or comments? Call us at 1-855-366-7755 (U.S.A. only) M-F 8am-5pm CST

Instruction

Children under 6 months of age, consult a medical professional before using this product.

For sudden onset of symptoms: Use every 15
minutes for up to 8 doses until symptoms relieved,
every 2 hours thereafter

Children Dose
6 - 18 lbs or 3 - 8 kgs 1.25 mL every 2 hours
19 - 29 lbs or 9 - 13 kgs 2.5 mL every 2 hours
30 - 90 lbs or 14 - 41 kgs 5 mL every 2 hours
*Reduce frequency when symptoms improve.

Warning

Warnings:

Stop use and ask doctor if:

- fever develops
- diarrhea lasts more than 2 days
- other symtomps persist for more than 7 days or worse

Usage

Temporarily relieves:

- Diarrhea
- Stomach Acid
- Gas & Bloating
- Upset Stomach
- Nervous Tummy

Purpose

Uses: Temporarily relieves infant discomfort caused by

- minor stomach pain
- upset stomach
- nervous tummy
- diarrhea
- colic
- gas
- indigestion
- excessive stomach acid
- nausea
- stomach presuure and cramps

Principal Display Panel

Label Display Panel